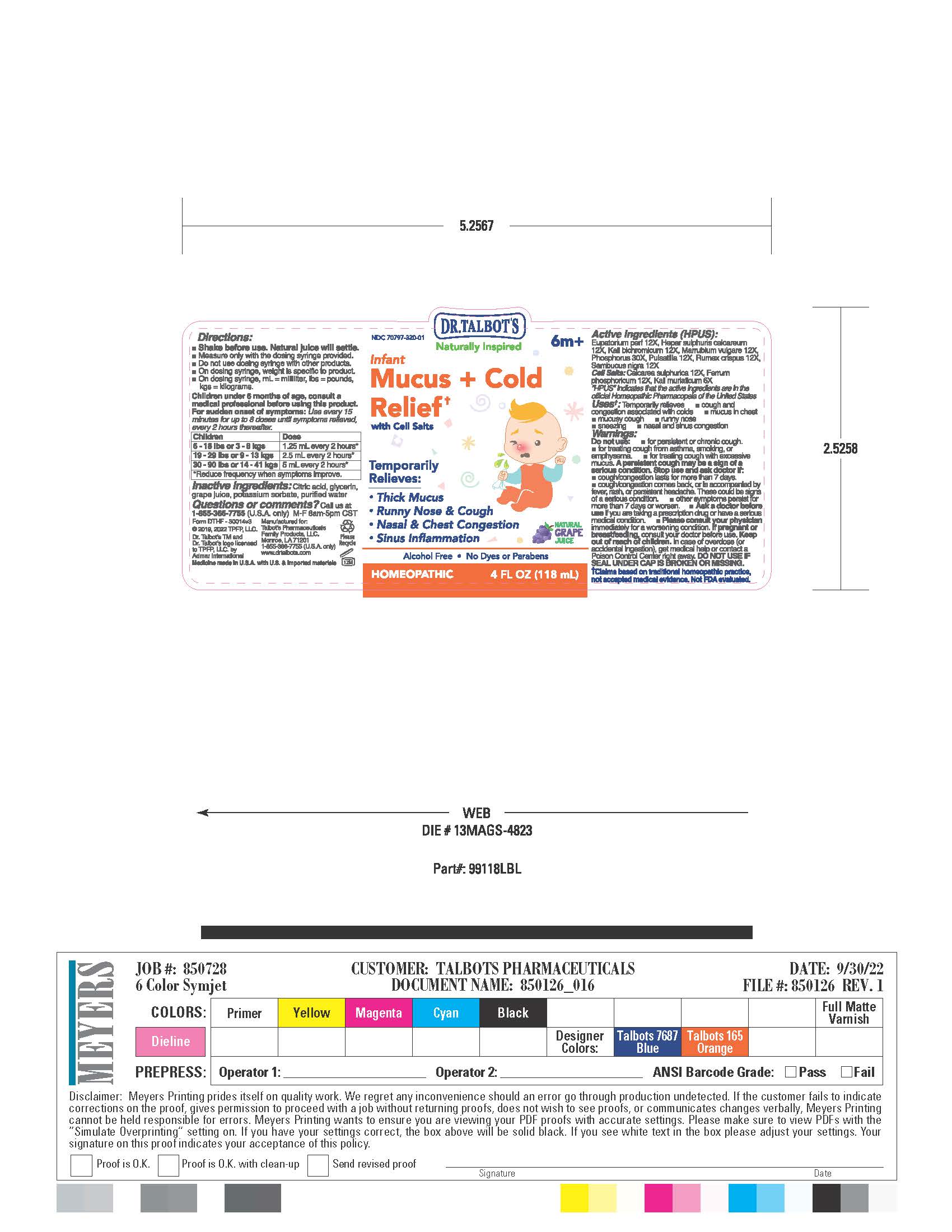 DRUG LABEL: Dr Talbots Infant Mucus Cold Relief
NDC: 70797-320 | Form: LIQUID
Manufacturer: Talbot’s Pharmaceuticals Family Products, LLC.
Category: homeopathic | Type: HUMAN OTC DRUG LABEL
Date: 20220913

ACTIVE INGREDIENTS: MARRUBIUM VULGARE 12 [hp_Q]/118 mL; SAMBUCUS NIGRA FLOWERING TOP 12 [hp_X]/118 mL; CALCIUM SULFATE ANHYDROUS 12 [hp_X]/118 mL; POTASSIUM CHLORIDE 6 [hp_X]/118 mL; EUPATORIUM PERFOLIATUM FLOWERING TOP 12 [hp_X]/118 mL; ANEMONE PULSATILLA 12 [hp_X]/118 mL; POTASSIUM DICHROMATE 12 [hp_X]/118 mL; CALCIUM SULFIDE 12 [hp_X]/118 mL; FERROSOFERRIC PHOSPHATE 12 [hp_X]/118 mL; RUMEX CRISPUS ROOT 12 [hp_X]/118 mL; PHOSPHORUS 30 [hp_X]/118 mL
INACTIVE INGREDIENTS: GLYCERIN; WATER; CITRIC ACID MONOHYDRATE; CONCORD GRAPE JUICE; POTASSIUM SORBATE

ACTIVE INGREDIENT

Active ingredients (HPUS)
Eupatorium perf 12X
Kali bichromicum 12X
Marrubium vulgare 12X
Phosphorus 30X
Pulsatilla 12X
Rumex crispus 12X
Sambucus nigra 12X

Cell Salts
Calcarea sulphurica 12X
Ferrum phosphoricum 12X
Kali muriaticum 6X

PREGNACY

Pregnant or breastfeeding

If pregnant or breastfeeding, consult your doctor before use.

Ask a doctor before use if you are taking a prescription drug or have a serious medical conditions.

Please counsult your physcian immidiately for a worsening condition.

INACTIVE INGREDIENTS

Citric acid, glycerin, grape juice, potassium
sorbate, purified water

QUESTIONS

Questions or comments?
Call us at 1-855-366-7755 (U.S.A. only)
M-F 8am-5pm CST

Warnings

Do not use:

- for persistent or chronic cough
- for treating cough from asthma, smoking, or emphysema
- for treating cough with excessive mucus.

A persistent may be a sign of a serious condition.

Stop use and ask doctor if:

- cough/congestion lasts for more than 7 days.
- cough/congestion comes back, or is accompanied by fever, rash, or persistent headache. these could be signs of a serious condition.
- other symptoms persist for more than 7 days or worsen.

Dosage

Children under 6 months of age, consult a
medical professional before using this product.
For sudden onset of symptoms: Use every 15 minutes for up to 8 doses until symptoms relieved, every 2 hours thereafter.

Children Dose
6 - 18 lbs or 3 - 8 kgs 1.25 mL every 2 hours*
19 - 29 lbs or 9 - 13 kgs 2.5 mL every 2 hours*
30 - 90 lbs or 14 - 41 kgs 5 mL every 2 hours*
*Reduce frequency when symptoms improve.

Keep out of reach of children. In case of overdose (or accidental ingestion), get medical help or contact a Poison Control Center right away. DO NOT USE IF SEAL UNDER CAP IS BROKEN OR MISSING.

Uses

Temporarily relieves

- cough and congestion associated with colds
- mucus in chest
- mucuy cough
- runny nose
- sneezing
- nasal and sinus congestion

Purpose

Temporarily Relieves:

- Thick Mucus
- Runny Nose & Cough
- Nasal & Chest Congestion
- Sinus Inflammation

PRICIPAL DISPLAY PANEL

Label: